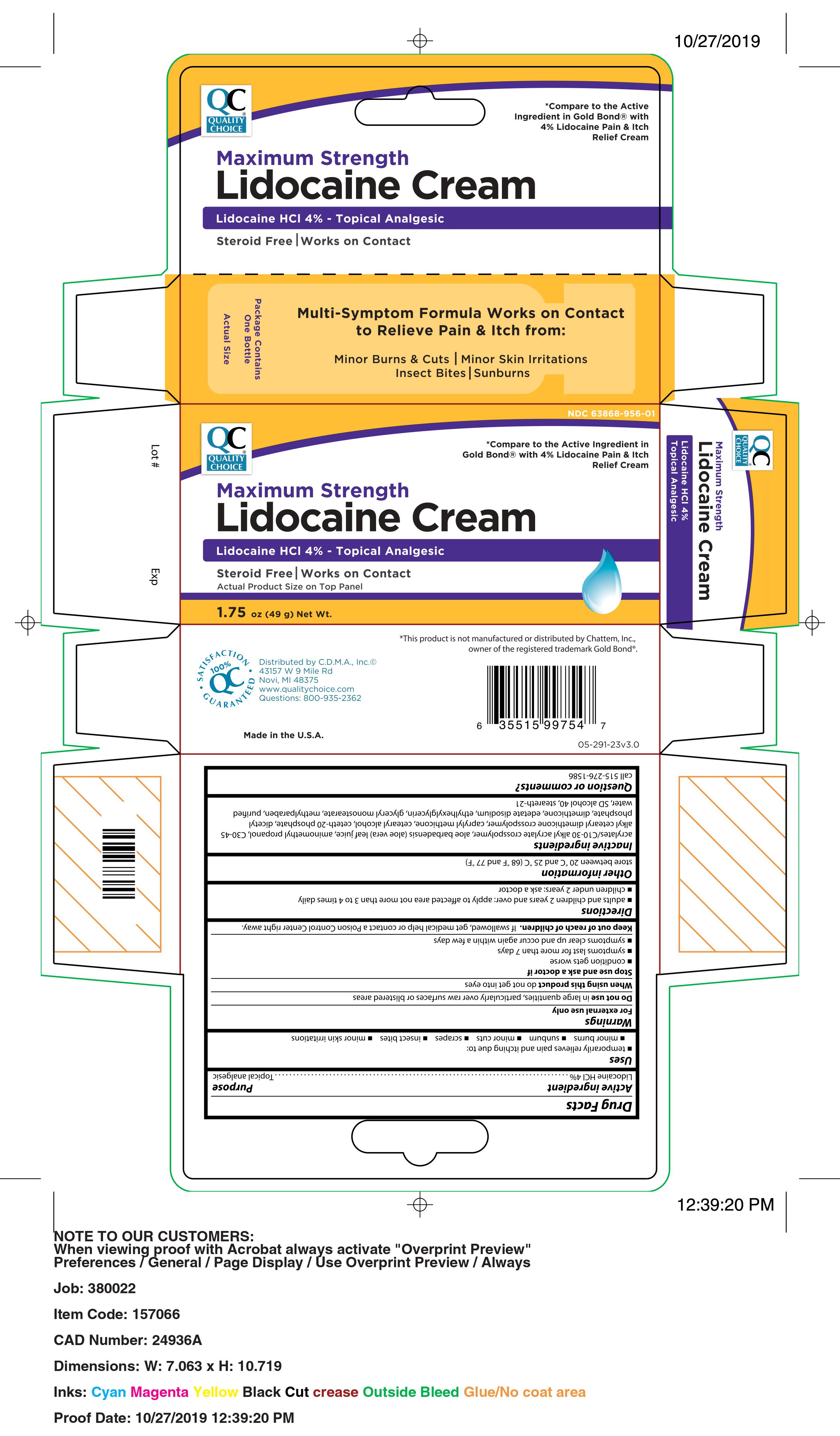 DRUG LABEL: QC Lidocaine
NDC: 63868-956 | Form: CREAM
Manufacturer: Chain Drug Marketing Association
Category: otc | Type: HUMAN OTC DRUG LABEL
Date: 20241208

ACTIVE INGREDIENTS: LIDOCAINE HYDROCHLORIDE 4 g/100 g
INACTIVE INGREDIENTS: STEARETH-21; GLYCERYL MONOSTEARATE; DIHEXADECYL PHOSPHATE; CETOSTEARYL ALCOHOL; CETETH-20 PHOSPHATE; ALCOHOL; CARBOMER INTERPOLYMER TYPE A (ALLYL SUCROSE CROSSLINKED); EDETATE DISODIUM; CAPRYLYL TRISILOXANE; ALOE VERA LEAF; WATER; AMINOMETHYLPROPANOL; DIMETHICONE; METHYLPARABEN; ETHYLHEXYLGLYCERIN

Quality Choice Lidocaine Cream

Active Ingredient

Lidocaine HCl 4%

Purpose

Topical analgesic

Uses

temporarily relieves pain and itching due to:

minor burns

sunburn

minor cuts

scrapes

insect bites

minor skin irritations

Warnings

For external use only

Do not use in large quantities, particularly over raw surfaces or blistered areas

When using this product do not get into eyes

Stop use and ask a doctor if

condition gets worse

symptoms last for more than 7 days

symptoms clear up and occur again within a few days

Keep out of reach of children

If swallowed, get medical help or contact a Poison Control Center right away.

Directions

adults and children 2 years and over: apply to affected area not more than 3 to 4 times daily

children under 2 years: ask a doctor

Other information

store between 20 °C and 25 °C

Inactive ingredients

acrylates/C10-30 alkyl acrylate crosspolymer, aloe barbadensis (aloe vera) leaf juice, aminomethyl propanol,
C30-45 alkyl cetearyl dimethicone crosspolymer, caprylyl methicone, cetearyl alcohol, ceteth-20 phosphate, dicetyl phosphate, dimethicone, edetate disodium, ethylhexylglycerin, glyceryl monostearate, methylparaben, purified water, SD alcohol 40, steareth-21

WHEN USING

do not get into eyes.

ASK DOCTOR

Conditions get worse

Symptoms last for more than 7 days or clears up and occurs again within a few days

KEEP OUT OF REACH OF CHILDREN

If swallowed, get medical help or contact Poison Control Center right away.

Prinicpal display panel

Quality Choice

Maximum Strength Lidocaine Cream Lidocaine HCL 4 %- Topical Analgesic

Steroid free, Works on Contact